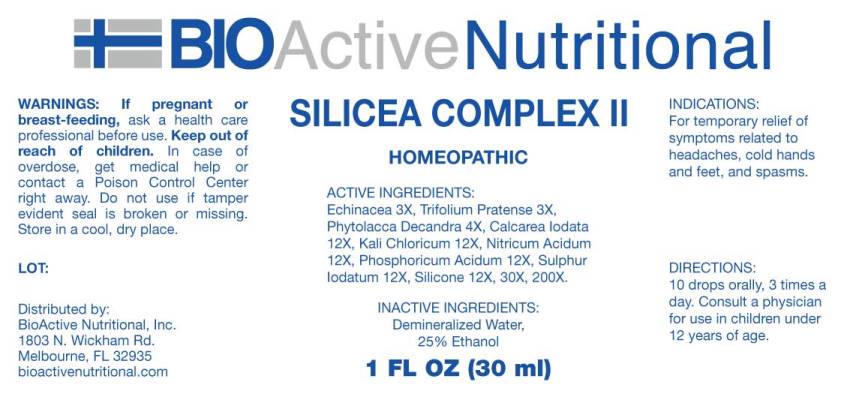 DRUG LABEL: SILICEA COMPLEX
NDC: 43857-0536 | Form: LIQUID
Manufacturer: BioActive Nutritional, Inc.
Category: homeopathic | Type: HUMAN OTC DRUG LABEL
Date: 20241018

ACTIVE INGREDIENTS: ECHINACEA ANGUSTIFOLIA WHOLE 3 [hp_X]/1 mL; TRIFOLIUM PRATENSE FLOWER 3 [hp_X]/1 mL; PHYTOLACCA AMERICANA ROOT 4 [hp_X]/1 mL; CALCIUM IODIDE 12 [hp_X]/1 mL; POTASSIUM CHLORATE 12 [hp_X]/1 mL; NITRIC ACID 12 [hp_X]/1 mL; PHOSPHORIC ACID 12 [hp_X]/1 mL; SULFUR IODIDE 12 [hp_X]/1 mL; DIMETHICONE 12 [hp_X]/1 mL
INACTIVE INGREDIENTS: WATER; ALCOHOL

DRUG FACTS:

ACTIVE INGREDIENTS:

Echinacea (Angustifolia) 3X, Trifolium Pratense 3X, Phytolacca Decandra 4X, Calcarea Iodata 12X, Kali Chloricum 12X, Nitricum Acidum 12X, Phosphoricum Acidum 12X, Sulphur Iodatum 12X, Silicone (Dimethicone)12X, 30X, 200X.

INDICATIONS:

For temporary relief of symptoms related to headaches, cold hands and feet, and spasms.

WARNINGS:

If pregnant or breast-feeding, ask a health care professional before use.

Keep out of reach of children. In case of overdose, get medical help or contact a Poison Control Center right away.

Do not use if tamper evident seal is broken or missing. Store in a cool, dry place.

Keep out of reach of children. In case of overdose, get medical attention or contact a Poison Control Center right away.

DIRECTIONS:

10 drops orally, 3 times a day. Consult a physician for use in children under 12 years of age.

INACTIVE INGREDIENTS:

Demineralized Water, 25% Ethanol

QUESTIONS:

Distributed by:

BioActive Nutritional, Inc.

1803 N. Wickham Rd.

Melbourne, FL 32935

bioactivenutritional.com

PACKAGE LABEL DISPLAY:

BioActive Homeopathic

SILICEA COMPLEX II

HOMEOPATHIC

1 FL OZ (30 ml)